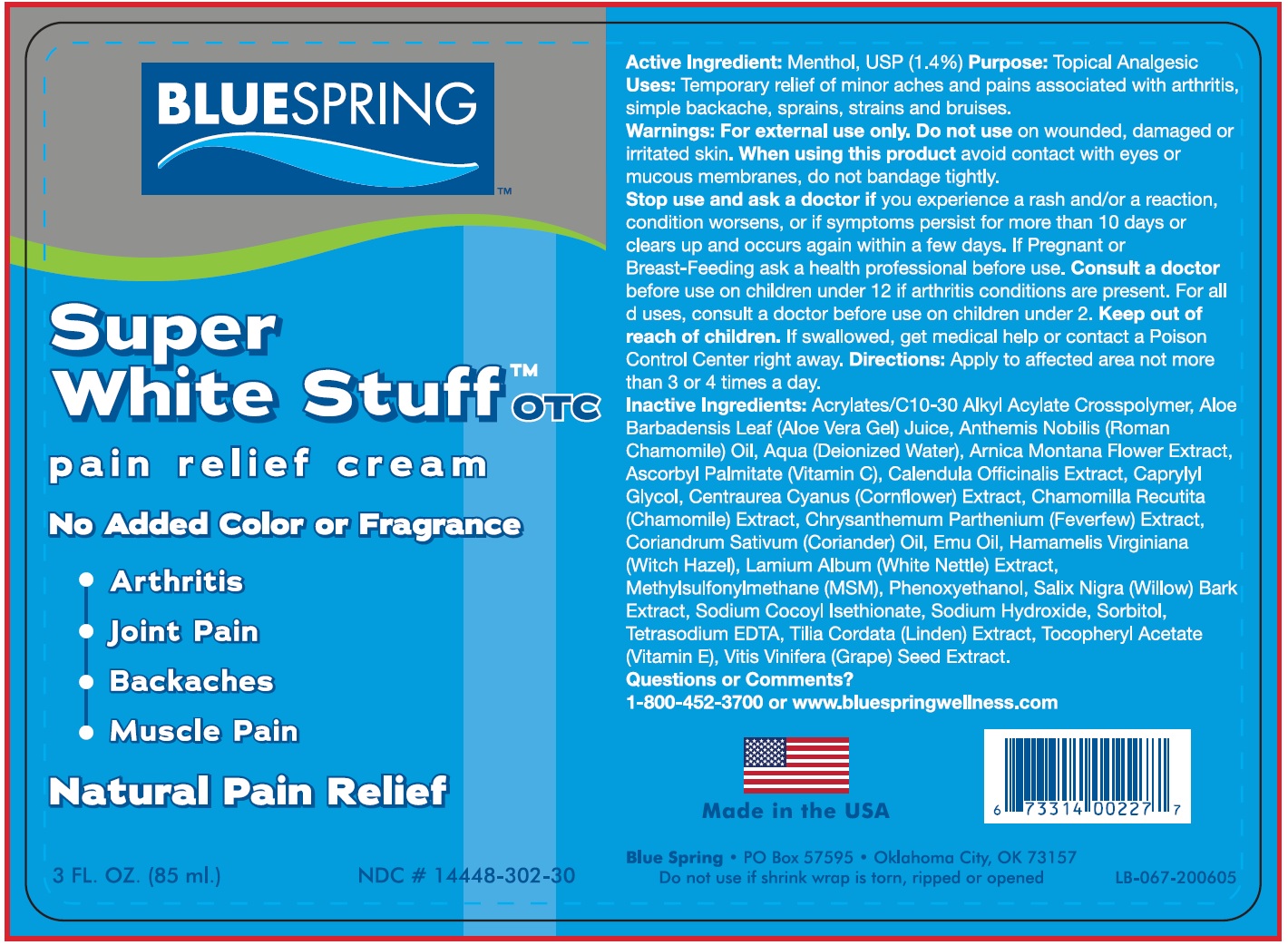 DRUG LABEL: SUPER WHITE STUFF Pain Relief
NDC: 14448-302 | Form: CREAM
Manufacturer: BLUE SPRING WELLNESS, L.L.C.
Category: otc | Type: HUMAN OTC DRUG LABEL
Date: 20231110

ACTIVE INGREDIENTS: MENTHOL 14 mg/1 mL
INACTIVE INGREDIENTS: CARBOMER INTERPOLYMER TYPE A (ALLYL SUCROSE CROSSLINKED); ALOE VERA LEAF; WATER; ARNICA MONTANA FLOWER; ASCORBYL PALMITATE; CALENDULA OFFICINALIS FLOWER; CAPRYLYL GLYCOL; CHAMOMILE; TANACETUM PARTHENIUM WHOLE; CORIANDER; EMU OIL; HAMAMELIS VIRGINIANA ROOT BARK/STEM BARK; LAMIUM ALBUM WHOLE; DIMETHYL SULFONE; PHENOXYETHANOL; SALIX NIGRA BARK; SODIUM COCOYL ISETHIONATE; SODIUM HYDROXIDE; SORBITOL; EDETATE SODIUM; TILIA CORDATA WHOLE; .ALPHA.-TOCOPHEROL ACETATE; VITIS VINIFERA SEED

SUPER WHITE STUFF Pain Relief Cream

Active Ingredient

Menthol, USP 1.4%

Purpose

Topical Analgesic

Uses

For the temporary relief of minor aches and pains associated with

- arthritis
- simple backahe
- sprains
- strains
- bruises

Warnings:

For external use only

Do not use

on wounded, damaged or irritated skin.

When using this product

- avoid contact with eyes or mucous membranes.
- Do not bandage tightly

Stop use and ask a doctor if

- you experience a rash and/or a reaction
- condition worsens or if symptoms persist for more than 10 days or clears up and occur again within a few days.

If Pregnant or Breast-Feeding

ask a health professional before use.

Consult a doctor

before use on children under 12 years of age if arthritis conditions are present. For all other listed uses, consult a doctor before use on children under 2 years of age.

Keep out of reach of children.

If swallowed, get medical help or contact a Poison Control Center right away.

Other information

Store at room temperature.

Directions

Apply to affected area not more than 3 to 4 times a days. before using for children under 12 for arthritic conditions and for all children under 2 years of age for all other uses. Consult a doctor

Inactive Ingrediets

Acrylates/C10-30 Alkyl Acrylate Crosspolymer, Aloe Barbadensis Leaf (Aloe Vera Gel) Juice, Anthemis Nobilis (Roman Chamomile) Oil, Aqua (Deionized Water), Arnica Montana Flower Extract, Ascorbyl Palmitate (Vitamin C), Calendula Officinalis Extract, Caprylyl Glycol, Centraurea Cyanus (Cornflower) Extract, Chamomilla Recutita (Chamomile) Extract, Chrysanthemum Parthenium (Feverfew) Extract, Coriandrum Sativum (Coriander) Oil, Emu Oil, Hamamelis Virginiana (Witch Hazel), Lamium Album (White Nettle) Extract, Methylsulfonylmethane (MSM), Phenoxyethanol, Salix Nigra (Willow) Bark Extract, Sodium Cocoyl Isethionate, Sodium Hydroxide, Sorbitol, Tetrasodium EDTA, Tilia Cordata (Linden) Extract, Tocopheryl Acetate (Vitamin E), Vitis Vinifera (Grape) Seed Extract.

Questions or Comments?

Call or visit www.bluestuff.com 1-800-452-3700